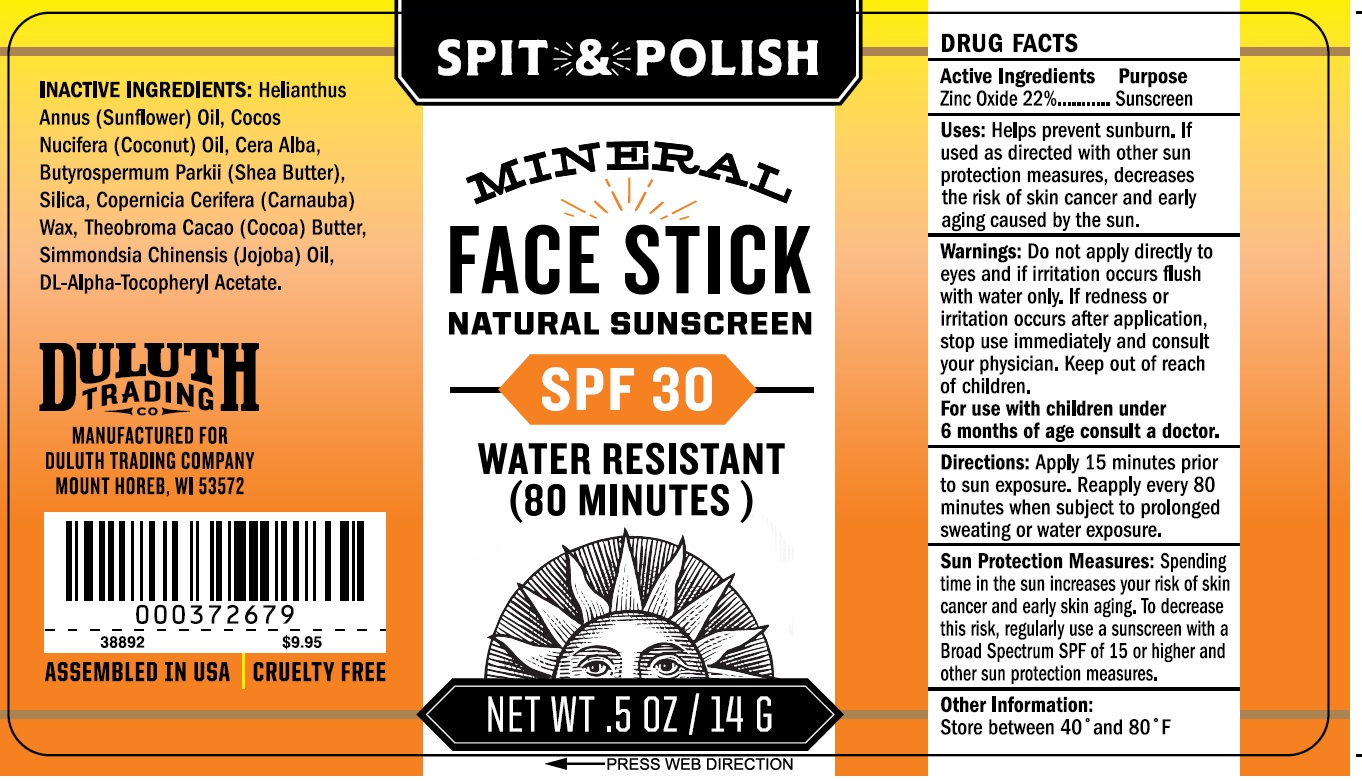 DRUG LABEL: Spit and Polish Mineral Face SPF 30
NDC: 80325-000 | Form: STICK
Manufacturer: Naturally Uncommon, LLC
Category: otc | Type: HUMAN OTC DRUG LABEL
Date: 20231109

ACTIVE INGREDIENTS: ZINC OXIDE 220 mg/1 g
INACTIVE INGREDIENTS: HELIANTHUS ANNUUS FLOWERING TOP; COCONUT OIL; WHITE WAX; SHEA BUTTER; SILICON DIOXIDE; CARNAUBA WAX; COCOA; JOJOBA OIL; .ALPHA.-TOCOPHEROL ACETATE, DL-

Spit & Polish Mineral Face Stick SPF 30

Active Ingredients

Zinc Oxide 22%

Purpose

Sunscreen

Uses

Helps prevent sunburn. If used as directed with other sun protection measures, decreases the risk of skin cancer and early aging caused by the sun.

Warnings:

Do not apply directly to eyes and if irritation occurs flush with water only. If redness or irritation occurs after application,

Stop use

immediately and consult your physician.

Keep out of reach of children.

For use with children under 6 months of age consult a doctor.

Directions:

Apply 15 minutes prior to sun exposure. Reapply every 80 minutes when subject to prolonged sweating or water exposure.

Spending time in the sun increases your risk of skin cancer and early skin aging. To decrease the risk, regularly use a sunscreen with a Broad Spectrum SPF of 15 or higher and other sun protection measures. Sun protection measures:

Other information:

Store between 40 ° and 80 ° F

INACTIVE INGREDIENTS:

Helianthus Annus (Sunflower) Oil, Cocos Nucifera (Coconut) Oil, Cera Alba, Butyrospermum Parkii (Shea Butter), Silica, Copernicia Cerifera (Carnauba) Wax, Theobroma Cacao (Cocoa) Butter, Simmondsia Chinensis (Jojoba) Oil, DL-Alpha-Tocopheryl Acetate.